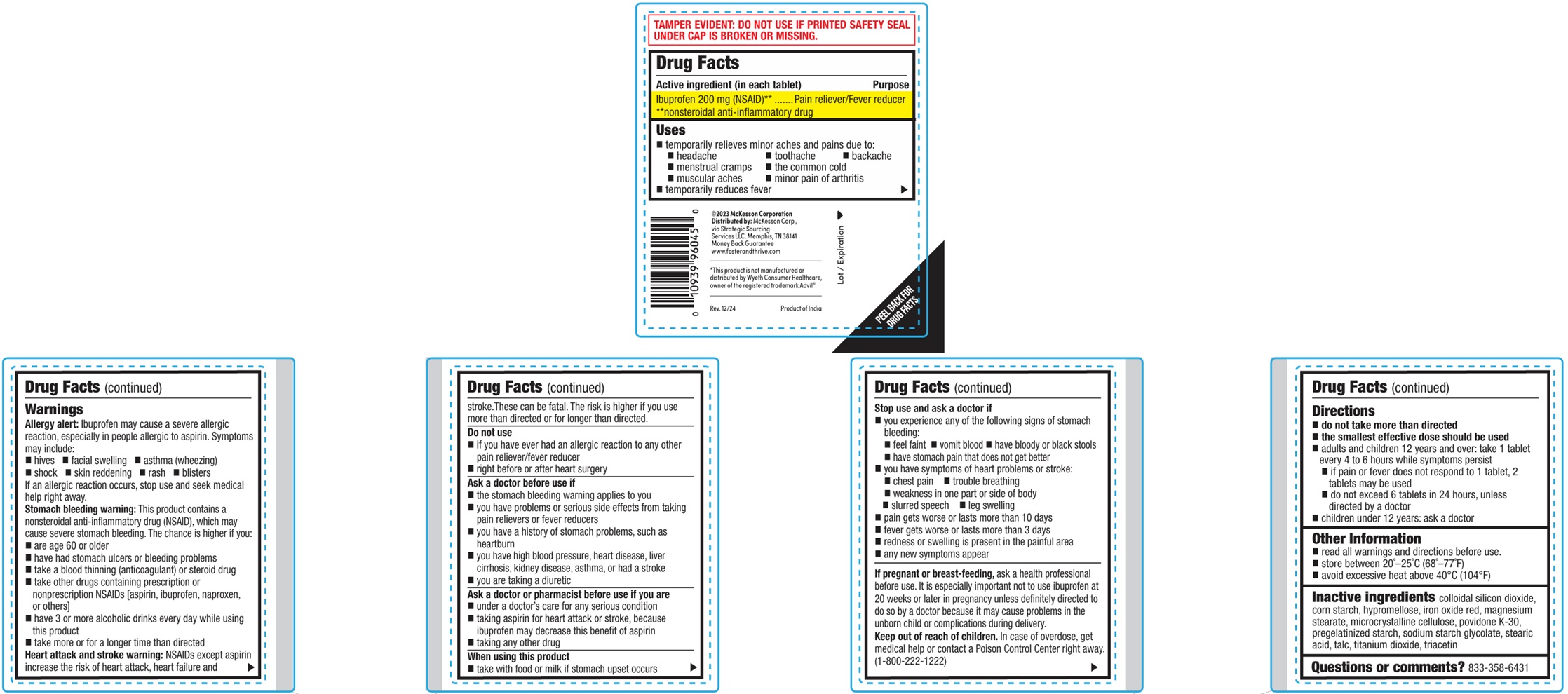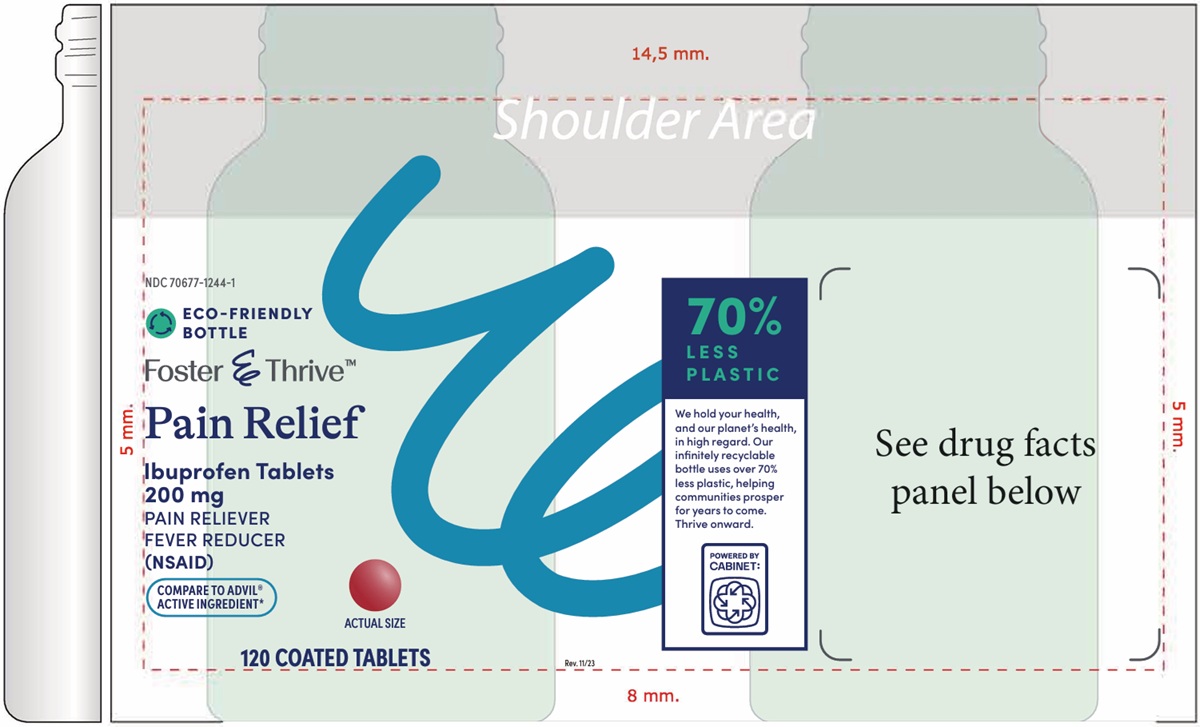 DRUG LABEL: Ibuprofen
NDC: 70677-1244 | Form: TABLET, FILM COATED
Manufacturer: Strategic Sourcing Services, LLC
Category: otc | Type: HUMAN OTC DRUG LABEL
Date: 20260129

ACTIVE INGREDIENTS: IBUPROFEN 200 mg/1 1
INACTIVE INGREDIENTS: SILICON DIOXIDE; STARCH, CORN; HYPROMELLOSES; FERRIC OXIDE RED; MAGNESIUM STEARATE; MICROCRYSTALLINE CELLULOSE; POVIDONE K30; STARCH, WHEAT; SODIUM STARCH GLYCOLATE TYPE A CORN; STEARIC ACID; TITANIUM DIOXIDE; TRIACETIN

Ibuprofen